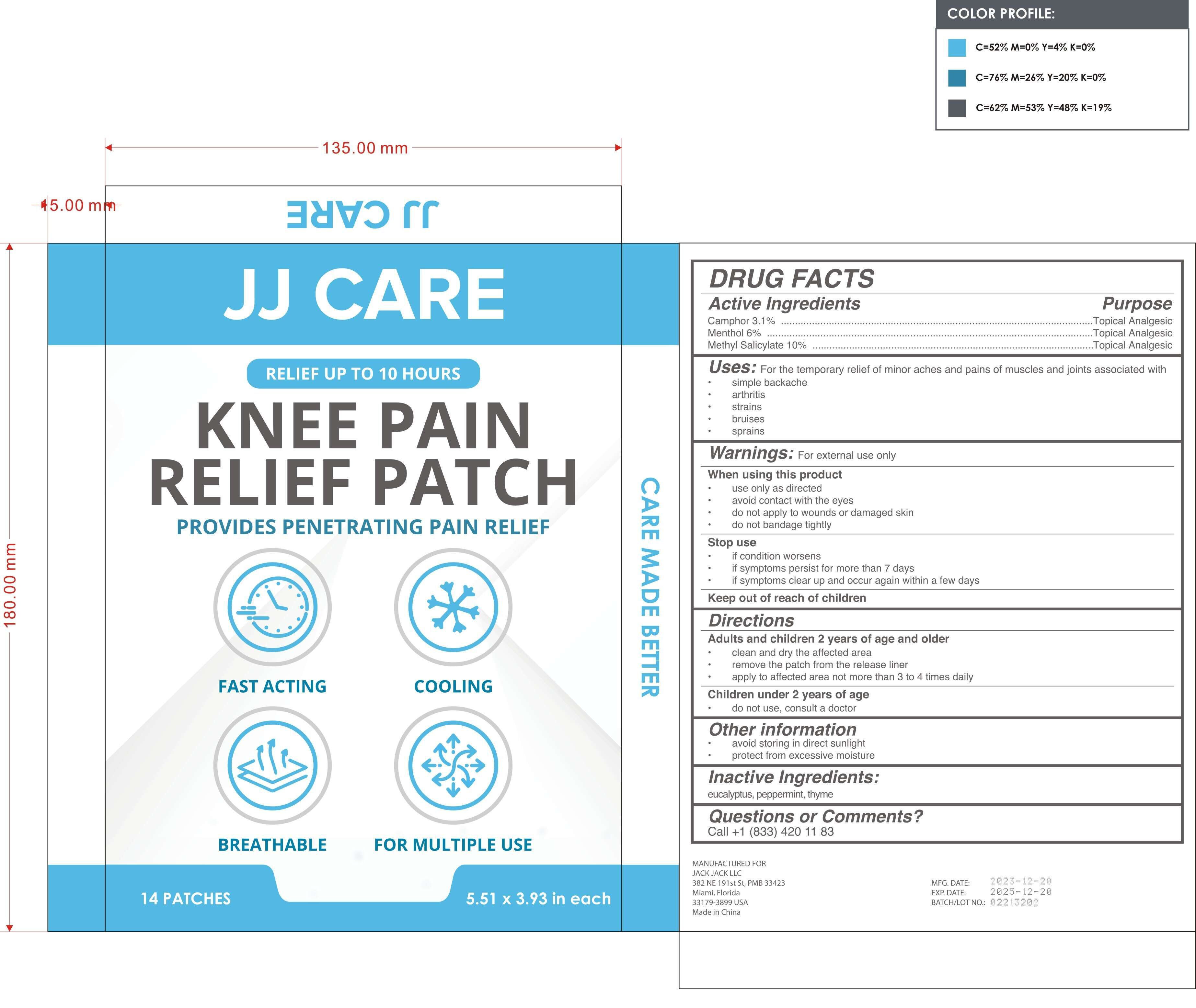 DRUG LABEL: Knee Pain Relief Patch
NDC: 81484-102 | Form: PATCH
Manufacturer: Anhui Miao De Tang Pharmaceutical Co., Ltd.
Category: otc | Type: HUMAN OTC DRUG LABEL
Date: 20240109

ACTIVE INGREDIENTS: METHYL SALICYLATE 10 g/100 1; CAMPHOR (SYNTHETIC) 3.1 g/100 1; MENTHOL 6 g/100 1
INACTIVE INGREDIENTS: PEPPERMINT; THYME; EUCALYPTUS OIL

Knee Pain Relief Patch

Knee Pain Relief Patch

ACTIVE INGREDIENT

camphor 3.1%
menthol 6%
methyl salicylate 10%

PURPOSE

For the temporary relief of minor aches and pains of muscles and joints associated with.
simple backache.
arthritis.
strains.
bruises.
sprains.

INDICATIONS AND USAGE

Adults and children 2 years of age and older
clean and dry the affected area.
remove the patch from the release liner.
apply to affected area not more than 3 to 4 times daily.

WARNINGS

For external use only

DO NOT USE

Children under 2 years of age
do not use, consult a doctor

WHEN USING

use only as directed.
avoid contact with the eyes.
do not apply to wounds or damaged skin.
do not bandage tightly.

STOP USE

if condition worsens.
if symptoms persist for more than 7 days.
if symptoms clear up and occur again within a few days.

Keep out of reach of children

DOSAGE AND ADMINISTRATION

apply to affected area not more than 3 to 4 times daily

STORAGE AND HANDLING

avoid storing in direct sunlight

protect from excessive moisture

INACTIVE INGREDIENT

eucalyptus, peppermint, thyme, wintergreen